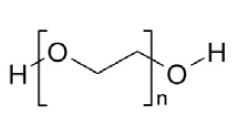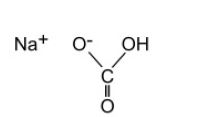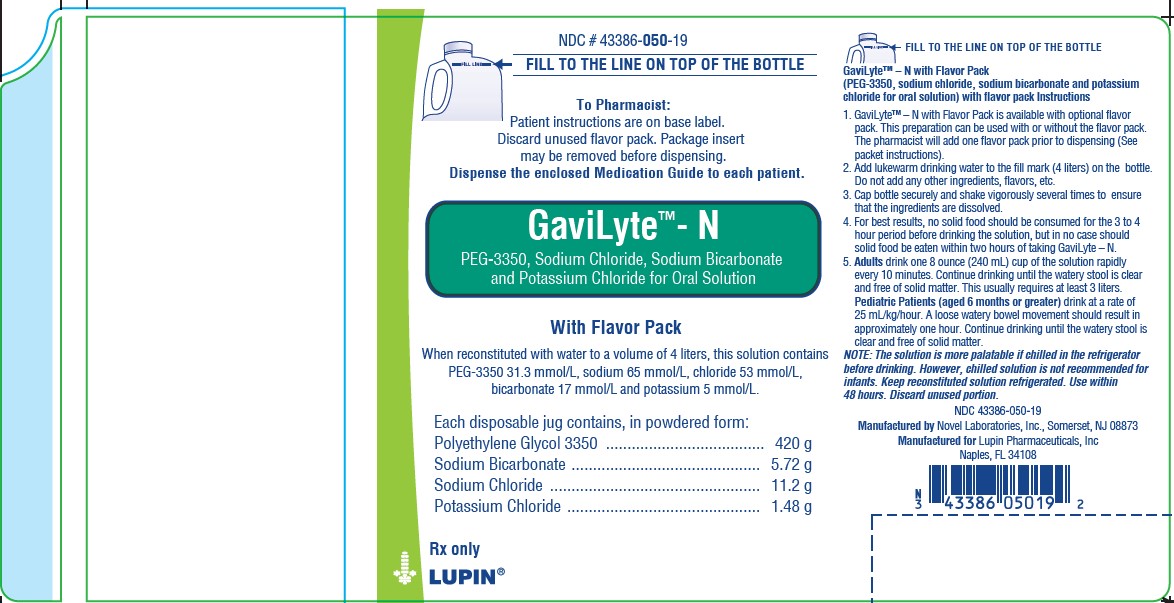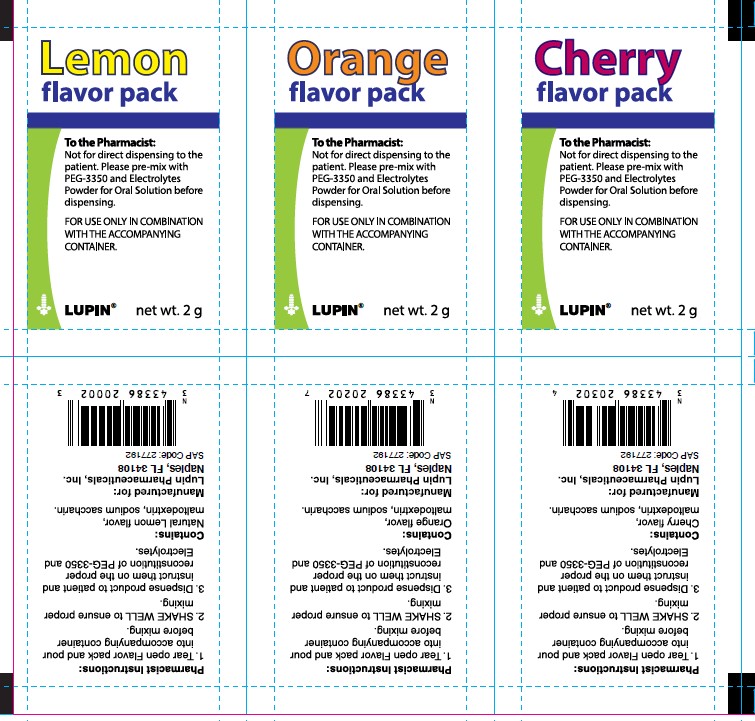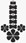 DRUG LABEL: GAVILYTE-N
NDC: 43386-050 | Form: POWDER, FOR SOLUTION
Manufacturer: Lupin Pharmaceuticals,Inc.
Category: prescription | Type: HUMAN PRESCRIPTION DRUG LABEL
Date: 20250910

ACTIVE INGREDIENTS: POLYETHYLENE GLYCOL 3350 420 g/438.4 g; SODIUM CHLORIDE 11.2 g/438.4 g; SODIUM BICARBONATE 5.72 g/438.4 g; POTASSIUM CHLORIDE 1.48 g/438.4 g
INACTIVE INGREDIENTS: SACCHARIN SODIUM; MALTODEXTRIN

HIGHLIGHTS OF PRESCRIBING INFORMATION

These highlights do not include all the information needed to use GaviLyte &ndash; N safely and effectively. See full prescribing information for GaviLyte &ndash; N
GaviLyte&trade; &ndash; N (polyethylene glycol 3350 (420 g), sodium chloride, sodium bicarbonate and potassium chloride for oral solution)
Initial U.S. Approval: 1991

RECENT MAJOR CHANGES

Warnings and Precautions, Aspiration: (5.7) 05/2021

1 INDICATIONS AND USAGE

GaviLyte-N is a combination of PEG 3350, an osmotic laxative, and electrolytes indicated for cleansing of the colon in preparation for colonoscopy in adults and pediatric patients aged 6 months or greater (1)

2 DOSAGE AND ADMINISTRATION

- GaviLyte-N, supplied as a powder, must be reconstituted with water before its use (2.1, 5.8)
- On day prior to colonoscopy, instruct patients to:
  - Eat a light breakfast or have clear liquids (avoid red and purple liquids) (2.2).
  - If adding a GaviLyte-N flavor pack, pour the contents of flavor powder (i.e., cherry, lemon or orange) into container prior to reconstitution (2.2).
  - Early in the evening prior to colonoscopy, fill container containing GaviLyte-N powder with lukewarm water to 4 liter fill line (2.2).
  - After capping container, shake vigorously several times (2.2).
- Instruct patients to consume water or clear liquids during and after bowel preparation up until 2 hours before time of colonoscopy (2.3).
- Adults: Drink at a rate of 240 mL (8 oz.) every 10 minutes, until 4 liters are consumed or rectal effluent is clear. For nasogastric tube (NGT), rate is 1.2 to 1.8 liters per hour (2.3)
- Pediatric patients (aged 6 months or greater): Drink 25 mL/kg/hour orally or administer by NGT. Continue drinking until watery stool is clear and free of solid matter (2.3).

3 DOSAGE FORMS AND STRENGTHS

For oral solution: polyethylene glycol 3350 420 grams, sodium bicarbonate 5.72 grams, sodium chloride 11.2 grams, potassium chloride 1.48 grams, and flavoring ingredients 2 grams; supplied in one 4 liter disposable jug(3)

4 CONTRAINDICATIONS

- Gastrointestinal (GI) obstruction, ileus, or gastric retention (4, 5.6)
- Bowel perforation (4, 5.6)
- Toxic colitis or toxic megacolon (4)
- Known allergy or hypersensitivity to components of GaviLyte-N (4, 11)

5 WARNINGS AND PRECAUTIONS

- Risk of fluid and electrolyte abnormalities, arrhythmias, seizures and renal impairment– assess concurrent medications and consider testing in some patients (5.1, 5.2,5.3, 5.4)
- Patients with renal insufficiency– use caution, ensure adequate hydration and consider testing (5.4)
- Suspected GI obstruction or perforation – rule out the diagnosis before administration (4, 5.6)
- Patients at risk for aspiration – observe during administration (5.7)
- Not for direct ingestion – dilute and take with additional water (5.8)

6 ADVERSE REACTIONS

Most common adverse reactions (≥3%) are: nausea, abdominal fullness and bloating. Abdominal cramps, vomiting and anal irritation occur less frequently (6)

To report SUSPECTED ADVERSE REACTIONS, contact Lupin Pharmaceuticals, Inc. at 1-866-403-7592 or FDA at 1-800-FDA-1088 or www.fda.gov/medwatch.

7 DRUG INTERACTIONS

- Some drugs increase risks due to fluid and electrolyte changes (7.1)
- Oral medication taken within 1 hour of start of each dose may not be absorbed properly (7.2)

FULL PRESCRIBING INFORMATION

1 INDICATIONS AND USAGE

GaviLyte-N is indicated for bowel cleansing prior to colonoscopy in adults and pediatric patients aged 6 months or greater.

2 DOSAGE AND ADMINISTRATION

2.1 Dosage Overview

- GaviLyte-N, supplied as a powder, must be reconstituted with water before its use; it is not for direct ingestion [see Dosage and Administration (2.2), Warnings and Precautions (5.8)].
- Do not reconstitute with other liquids and/or add starch-based thickeners to the mixing container [see Warnings and Precautions (5.7)].
- The 4-liter reconstituted GaviLyte-N solution contains: 420 grams of polyethylene glycol (PEG) 3350, 5.72 grams of sodium bicarbonate, 11.2 grams of sodium chloride, and 1.4 grams of potassium chloride. GaviLyte-N may be used with or without one of the supplied flavor packs.

2.2 Administration Instructions Prior to Dosage

On the day prior to the colonoscopy, instruct patients to:

1. Take only clear liquids, but avoid red and purple liquids. Patients may consume a light breakfast.
2. If adding a GaviLyte-N flavor pack, pour the contents of the 2 gram flavor powder (i.e., cherry, lemon, or orange) into the container prior to reconstitution. No additional flavorings should be added. Discard unused flavor packs. The GaviLyte-N flavor packs are for use only in combination with the contents of the accompanying 4 liter container.
3. Early in the evening prior to colonoscopy, fill the supplied container containing the GaviLyte-N powder (and if applicable, a flavor powder) with lukewarm water (to facilitate dissolution) to the 4 liter fill line. The solution is clear and colorless when reconstituted to a final volume of 4 liters.
4. After capping the container, shake vigorously several times to ensure that the ingredients are dissolved. When reconstituted use within 48 hours.

2.3 Dosage

The following is the recommended dose of reconstituted GaviLyte-N solution for adults and pediatric patients ≥ 6 months. Instruct patients they may consume water or clear liquids during the bowel preparation and after completion of the bowel preparation up until 2 hours before the time of the colonoscopy. The solution is more palatable if chilled prior to administration.

- Adults: Instruct patients to drink a total of up to 4 liters at a rate of 240 mL (8 oz.) every 10 minutes, until 4 liters are consumed or the rectal effluent is clear. Rapid drinking of each portion is preferred to drinking small amounts continuously. For NGT, rate is 20 -30 mL per minute (1.2 – 1.8 liters per hour).
- Pediatric Patients ≥ 6 Months: Pediatric patients should drink 25 mL/kg/hour until the stool is watery, clear, and free of solid matter. If pediatric patients are unable to drink the reconstituted GaviLyte-N solution, the solution may be given by nasogastric (NGT). NGT administration is at the rate of 25 mL/kg/hour.

The first bowel movements should occur approximately one hour after the start of GaviLyte-N administration. Continue drinking until the watery stool is clear and free of solid matter.

3 DOSAGE FORMS AND STRENGTHS

For oral solution: One 4 liter jug with powder for reconstitution with water.

Each 4 liter jug contains: polyethylene glycol 3350 420 g, sodium bicarbonate 5.72 g, sodium chloride 11.2 g, potassium chloride 1.48 g and flavoring ingredients 2 g. When made up to 4 liters volume with water, the solution contains PEG-3350 31.3 mmol/L, sodium 65 mmol/L, chloride 53 mmol/L, bicarbonate 17 mmol/L and potassium 5 mmol/L.

4 CONTRAINDICATIONS

GaviLyte-N is contraindicated in the following conditions:

- Gastrointestinal (GI) obstruction, ileus, or gastric retention
- Bowel perforation
- Toxic colitis or toxic megacolon
- Known allergy or hypersensitivity to any component of GaviLyte-N for oral solution [see How Supplied/Storage and Handling (16)]

5 WARNINGS AND PRECAUTIONS

5.1 Serious Fluid and Serum Chemistry Abnormalities

Advise patients to hydrate adequately before, during, and after the use of GaviLyte-N. Use caution in patients with congestive heart failure when replacing fluids. If a patient develops significant vomiting or signs of dehydration including signs of orthostatic hypotension after taking GaviLyte-N, consider performing post-colonoscopy lab tests (electrolytes, creatinine, and BUN) and treat accordingly. Fluid and electrolyte disturbances can lead to serious adverse events including cardiac arrhythmias, seizures and renal impairment. Fluid and electrolyte abnormalities should be corrected before treatment with GaviLyte-N.

In addition, use caution when prescribing GaviLyte-N for patients who have conditions, or who are using medications, that increase the risk for fluid and electrolyte disturbances or may increase the risk of adverse events of seizure, arrhythmias, and renal impairment [see Drug Interactions (7.1)]

5.2 Cardiac Arrhythmias

There have been rare reports of serious arrhythmias associated with the use of ionic osmotic laxative products for bowel preparation. Use caution when prescribing GaviLyte-N for patients at increased risk of arrhythmias (e.g., patients with a history of prolonged QT, uncontrolled arrhythmias, recent myocardial infarction, unstable angina, congestive heart failure, or cardiomyopathy). Pre-dose and post-colonoscopy ECGs should be considered in patients at increased risk of serious cardiac arrhythmias.

5.3 Seizures

There have been reports of generalized tonic-clonic seizures and/or loss of consciousness associated with use of bowel preparation products in patients with no prior history of seizures. The seizure cases were associated with electrolyte abnormalities (e.g., hyponatremia, hypokalemia, hypocalcemia, and hypomagnesemia) and low serum osmolality. The neurologic abnormalities resolved with correction of fluid and electrolyte abnormalities.

Use caution when prescribing GaviLyte-N for patients with a history of seizures and in patients at increased risk of seizure, such as patients taking medications that lower the seizure threshold (e.g., tricyclic antidepressants), patients withdrawing from alcohol or benzodiazepines, or patients with known or suspected hyponatremia.

5.4 Renal Impairment

Use caution when prescribing GaviLyte-N for patients with impaired renal function or patients taking concomitant medications that may affect renal function (such as diuretics, angiotensin converting enzyme inhibitors, angiotensin receptor blockers, or non-steroidal anti-inflammatory drugs). Advise these patients of the importance of adequate hydration, and consider performing baseline and post-colonoscopy laboratory tests (electrolytes, creatinine, and BUN) in these patients.

5.5 Colonic Mucosal Ulcerations and Ischemic Colitis

Administration of osmotic laxative products may produce colonic mucosal aphthous ulcerations, and there have been reports of more serious cases of ischemic colitis requiring hospitalization. Concurrent use of stimulant laxatives and GaviLyte-N may increase this risk. The potential for mucosal ulcerations resulting from the bowel preparation should be considered when interpreting colonoscopy findings in patients with known or suspect inflammatory bowel disease (IBD).

5.6 Use in Patients with Significant Gastrointestinal Disease

If gastrointestinal obstruction or perforation is suspected, perform appropriate diagnostic studies to rule out these conditions before administering GaviLyte-N. If a patient experiences severe bloating, distention or abdominal pain, administration should be slowed or temporarily discontinued until the symptoms abate. If gastrointestinal obstruction or perforation is suspected, appropriate studies should be performed to rule out these conditions before administration of GaviLyte-N. Use with caution in patients with severe active ulcerative colitis.

5.7 Aspiration

Use with caution in patients with impaired gag reflex, unconscious, or semiconscious patients, and patients prone to regurgitation or aspiration. Such patients should be observed during administration of GaviLyte-N, especially if it is administered via nasogastric tube.

Do not combine GaviLyte- N with starch-based thickeners [see Dosage and Administration (2.1)]. Polyethylene glycol (PEG), a component of GaviLyte - N, when mixed with starch-thickened liquids reduces the viscosity of the starch-thickened liquid. When a PEG-based product used for another indication was mixed in starch-based pre-thickened liquids used in patients with dysphagia, thinning of the liquid occurred and cases of choking and potential aspiration were reported.

5.8 Not for Direct Ingestion

The contents of each jug must be diluted with water to a final volume of 4 liters (4 L) and ingestion of additional water is important to patient tolerance. Direct ingestion of the undissolved powder may increase the risk of nausea, vomiting, dehydration, and electrolyte disturbances.

6 ADVERSE REACTIONS

The following serious or otherwise important adverse reactions are described elsewhere in the labeling:

- Serious Fluid and Serum Chemistry Abnormalities [see Warnings and Precautions (5.1)] .
- Cardiac Arrhythmias [see Warnings and Precautions (5.2)] .
- Seizures [see Warnings and Precautions (5.3)] .
- Renal Impairment [see Warnings and Precautions (5.4)] .
- Colonic Mucosal Ulcerations, Ischemic Colitis and Ulcerative Colitis [see Warnings and Precautions (5.5)] .
- Patients with Significant Gastrointestinal Disease [see Warnings and Precautions (5.6)] .
- Aspiration [see Warnings and Precautions (5.7)] .
- Direct Ingestion [see Warnings and Precautions (5.8)] .

The following adverse reactions have been identified during post-approval use of GaviLyte-N. Because these reactions are reported voluntarily from a population of uncertain size, it is not always possible to reliably estimate their frequency or establish a causal relationship to drug exposure.

Nausea, abdominal fullness and bloating are the most common adverse reactions (occurred in up to 50% of patients) to administration of GaviLyte-N. Abdominal cramps, vomiting and anal irritation occur less frequently. These adverse reactions are transient and usually subside rapidly. Isolated cases of urticaria, rhinorrhea, dermatitis and (rarely) anaphylactic reaction have been reported which may represent allergic reactions.

Published literature contains isolated reports of serious adverse reactions following the administration of PEG-electrolyte solution products in patients over 60 years of age. These adverse events include upper GI bleeding from Mallory-Weiss Tear, esophageal perforation, asystole, sudden dyspnea with pulmonary edema, and "butterfly-like" infiltrates on chest X-ray after vomiting and aspirating PEG.

7 DRUG INTERACTIONS

7.1 Drugs that May Lead to Fluid and Electrolyte Abnormalities

Use caution when prescribing GaviLyte-N for patients who are using medications that increase the risk for fluid and electrolyte disturbances or may increase the risk of adverse events of seizure, arrhythmias, and prolonged QT in the setting of fluid and electrolyte abnormalities. Consider additional patient evaluations as appropriate [see Warnings and Precautions (5.1, 5.2, 5.3, and 5.4)] in patients taking these concomitant medications.

7.2 Potential for Altered Drug Absorption

Oral medication administered within one hour of the start of administration of GaviLyte-N may be flushed from the gastrointestinal tract and the medication may not be absorbed properly.

7.3 Stimulant Laxatives

Concurrent use of stimulant laxatives and GaviLyte-N may increase the risk of mucosal ulceration or ischemic colitis. Avoid use of stimulant laxatives (e.g., bisacodyl, sodium picosulfate) while taking GaviLyte-N.

8 USE IN SPECIFIC POPULATIONS

8.1 Pregnancy

Animal reproduction studies have not been conducted with GaviLyte-N. It is also not known whether GaviLyte-N can cause fetal harm when administered to a pregnant woman or can affect reproductive capacity. GaviLyte-N should be given to a pregnant woman only if clearly needed.

8.3 Nursing Mothers

It is not known whether this drug is excreted in human milk. Because many drugs are excreted in human milk, caution should be exercised when GaviLyte-N is administered to a nursing woman.

8.4 Pediatric Use

Safety and effectiveness of GaviLyte-N in pediatric patients aged 6 months and older is supported by evidence from adequate and well-controlled clinical trials of GaviLyte-N in adults with additional safety and efficacy data from published studies of similar formulations. Use of GaviLyte-N in children younger than 2 years of age should be carefully monitored for occurrence of possible hypoglycemia, as this solution has no caloric substrate. Dehydration has been reported in one child and hypokalemia has been reported in 3 children.

8.5 Geriatric Use

Clinical studies of GaviLyte-N did not include sufficient numbers of subjects aged 65 and over to determine whether they respond differently from younger subjects. Other reported clinical experience has not identified differences in responses between the elderly and younger patients.

11 DESCRIPTION

For oral solution: Each 4 liter (4L) GaviLyte-N jug contains a white powder for reconstitution. GaviLyte-N is a combination of polyethylene glycol 3350, an osmotic laxative, and electrolytes (sodium chloride, sodium bicarbonate and potassium chloride) for oral solution.

Each 4 liter jug contains: polyethylene glycol 3350 420g, sodium bicarbonate 5.72 g, sodium chloride 11.2 g, potassium chloride 1.4 g. The solution is clear and colorless when reconstituted to a final volume of 4 liters with water.

Polyethylene Glycol 3350, NF

Sodium Bicarbonate, USP

The chemical name is NaHCO3. The average Molecular Weight is 84.01. The structural formula is:

Sodium Chloride, USP

The chemical name is NaCl. The average Molecular Weight: 58.44. The structural formula is:

Na+ Cl-

Potassium Chloride, USP

The chemical name is KCl. The average Molecular Weight: 74.55. The structural formula is:

K-Cl

12 CLINICAL PHARMACOLOGY

12.1 Mechanism of Action

The primary mode of action is thought to be through the osmotic effect of polyethylene glycol 3350 which causes water to be retained in the colon and produces a watery stool.

12.2 Pharmacodynamics

GaviLyte-N induces as diarrhea which rapidly cleanses the bowel, usually within four hours.

12.3 Pharmacokinetics

The pharmacokinetics of PEG3350 following administration of GaviLyte-N were not assessed. Available pharmacokinetic information for oral PEG3350 suggests that it is poorly absorbed.

13 NONCLINICAL TOXICOLOGY

13.1 Carcinogenesis, Mutagenesis, Impairment of Fertility

Long term studies in animals have not been performed to evaluate carcinogenic potential of GaviLyte-N. Studies to evaluate the possible impairment of fertility or mutagenic potential of GaviLyte-N have not been performed.

16 HOW SUPPLIED/STORAGE AND HANDLING

In powdered form, for oral administration as a solution following reconstitution. GaviLyte-N is available in a disposable jug in powdered form containing:

GaviLyte-N with Flavor Packs: polyethylene glycol 3350 420 g, sodium bicarbonate 5.72 g, sodium chloride 11.2 g, potassium chloride 1.48 g and flavoring ingredients 2.0 g (optional). When made up to 4 liters volume with water, the solution contains PEG-3350 31.3 mmol/L, sodium 65 mmol/L, chloride 53 mmol/L, bicarbonate 17 mmol/L and potassium 5 mmol/L. Each jug has an attached package containing 3 flavor packs (optional); one each 2.0 g: Cherry, Lemon, and Orange flavoring, in powdered form, for the addition of ONE pack by the pharmacist prior to dispensing.

Lemon Flavor GaviLyte-N: polyethylene glycol 3350 420 g, sodium bicarbonate 5.72 g, sodium chloride 11.2 g, potassium chloride 1.48 g and flavoring ingredients 2.0 g. When made up to 4 liters volume with water, the solution contains PEG-3350 31.3 mmol/L, sodium 65 mmol/L, chloride 53 mmol/L, bicarbonate 17 mmol/L and potassium 5 mmol/L.

Storage:

Store at 25°C (77°F); excursions permitted to 15-30°C (59-86°F) [see USP Controlled Room Temperature]. When reconstituted, keep solution refrigerated. Use within 48 hours. Discard unused portion.

Keep out of reach of children.

GaviLyte-N with Flavor Packs NDC 43386-050-19

17 PATIENT COUNSELING INFORMATION

See FDA-Approved Patient Labeling (Medication Guide). Instruct patients:

- To let you know if they have trouble swallowing or are prone to regurgitation or aspiration.
- Not to take other laxatives while they are taking GaviLyte-N.
- To consume water or clear liquids during the bowel preparation and after completion of the bowel preparation up until 2 hours before the time of the colonoscopy.
- That if they experience severe bloating, distention or abdominal pain, the administration of the solution should be slowed or temporarily discontinued until the symptoms abate. Advise patients to report these events to their health care provider.
- That if they have hives, rashes, or any allergic reaction, they should discontinue the medication and contact their health care provider. Medication should be discontinued until they speak to their physician.
- To contact their healthcare provider if they develop signs and symptoms of dehydration [see Warnings and Precautions (5.1)].
- That oral medication administered within one hour of the start of administration of GaviLyte-N solution may be flushed from the GI tract and the medication may not be absorbed completely.

LUPIN and the are registered trademarks of Lupin Pharmaceuticals, Inc.

Manufactured by:

Novel Laboratories, Inc.

Somerset, NJ 08873

Manufactured for:

Lupin Pharmaceuticals, Inc.

Naples FL, 34108

SAP Code: 276329

Rev. 11/2024

MEDICATION GUIDE

GaviLyte™- N (GAV-ee-LITE-N)

(polyethylene glycol 3350 (420 g), sodium chloride, sodium bicarbonate and potassium chloride oral solution)

Read this Medication Guide before you start taking GaviLyte-N. This information does not take the place of talking with your healthcare provider about your medical condition or your treatment.

What is the most important information I should know about GaviLyte-N?

GaviLyte-N and other osmotic bowel preparations can cause serious side effects, including:

Serious loss of body fluid (dehydration) and changes in blood salts (electrolytes) in your blood.

These changes can cause:

- abnormal heartbeats that can cause death
- seizures . This can happen even if you have never had a seizure.
- kidney problems

Your chance of having fluid loss and changes in body salts with GaviLyte-N is higher if you:

- have heart problems
- have kidney problems
- take water pills or non-steroidal anti-inflammatory drugs (NSAIDS)

Tell your healthcare provider right away if you have any of these symptoms of a loss of too much body fluid (dehydration) while taking GaviLyte-N:

- vomiting that prevents you from keeping down the solution
- dizziness
- urinating less often than normal
- headache

See Section "What are the possible side effects of GaviLyte-N" for more information about side effects.

What is GaviLyte-N?

GaviLyte-N is a prescription medicine used by adults to clean the colon before a colonoscopy. GaviLyte-N cleans your colon by causing you to have diarrhea. Cleaning your colon helps your healthcare provider see the inside of your colon more clearly during your colonoscopy.

GaviLyte-N is safe and effective for use in pediatric patients aged 6 months and older.

Who should not take GaviLyte-N?

Do not take GaviLyte-N if your healthcare provider has told you that you have:

- a blockage in your bowel (obstruction)
- an opening in the wall of your stomach or intestine (bowel perforation)
- problems with food and fluid emptying from your stomach (gastric retention)
- a very dilated intestine (bowel)
- an allergy to any of the ingredients in GaviLyte-N. See the end of this leaflet for a complete list of ingredients in GaviLyte-N.

What should I tell my healthcare provider before taking GaviLyte-N?

Before you take GaviLyte-N, tell your healthcare provider if you:

- have heart problems
- have stomach or bowel problems
- have ulcerative colitis
- have problems with swallowing or gastric reflux
- have a history of seizures
- are withdrawing from drinking alcohol
- have a low blood salt (sodium) level
- have kidney problems
- any other medical conditions
- are pregnant. It is not known if GaviLyte-N will harm your unborn baby.

Talk to your doctor if you are pregnant or plan to become pregnant.

- are breastfeeding or plan to breastfeed. It is not known if GaviLyte-N passes into your breast milk. You and your healthcare provider should decide if you will take GaviLyte-N while breastfeeding.

Tell your healthcare provider about all the medicines you take, including prescription and non-prescription medicines, vitamins, and herbal supplements.

GaviLyte-N may affect how other medicines work. Medicines taken by mouth may not be absorbed properly when taken within 1 hour before the start of GaviLyte-N.

Especially tell your healthcare provider if you take:

- medicines for blood pressure or heart problems
- medicines for kidney problems
- medicines for seizures
- water pills (diuretics)
- non-steroidal anti-inflammatory medicines (NSAID) pain medicines
- laxatives
- starch-based thickeners. For patients who have trouble swallowing, do not mix GaviLyte-N with starch-based thickeners.

Ask your healthcare provider or pharmacist for a list of these medicines if you are not sure if you are taking any of the medicines listed above.

Know the medicines you take. Keep a list of them to show your healthcare provider and pharmacist when you get a new medicine.

How should I take GaviLyte-N?

You must read, understand, and follow these instructions to take GaviLyte-N the right way.

- Take GaviLyte-N exactly as your healthcare provider tells you to take it.
- Drink 240 mL (8 oz.) every 10 minutes. Rapid drinking of each portion is better than drinking small amounts.
- The first bowel movement should occur approximately one hour after you start drinking the solution.
- You may experience some abdominal bloating and distention before the bowels start to move. If severe discomfort or distention occur, stop drinking temporarily or drink each portion at longer intervals until the discomfort goes away.
- Continue drinking until the watery stool is clear and free of solid matter. This usually requires 3 liters and it is best to drink all of the solution.
- Do not take undissolved GaviLyte-N powder that has not been mixed with water (diluted), it may increase your risk of nausea, vomiting and fluid loss (dehydration).
- Each jug of GaviLyte-N must be reconstituted with water (diluted) to 4 liters total volume before drinking.
- Do not take other laxatives while taking GaviLyte-N.
- Do not eat solid foods on the day before your colonoscopy and until after your colonoscopy . Drink only clear liquids:
  - the day before your colonoscopy
  - while taking GaviLyte-N
  - after taking GaviLyte-N until 2 hours before your colonoscopy

What are the possible side effects of GaviLyte-N?

GaviLyte-N can cause serious side effects, including:

- See Section "What is the most important information I should know about GaviLyte-N?"
- changes in certain blood tests . Your healthcare provider may do blood tests after you take GaviLyte-N to check your blood for changes. Tell your healthcare provider if you have any symptoms of too much fluid loss, including:
  - vomiting
  - nausea
  - bloating
  - dizziness
  - stomach (abdominal) cramping
  - headache
  - urinate less than usual
  - trouble drinking clear liquid

- heart problems. GaviLyte-N may cause irregular heartbeats.
- seizures
- ulcers of the bowel or bowel problems (ischemic colitis). Tell your healthcare provider right away if you have severe stomach-area (abdomen) pain or rectal bleeding.

The most common side effects of GaviLyte-N include:

- nausea
- stomach (abdominal) fullness
- bloating
- stomach (abdominal) cramps
- vomiting
- anal irritation

Tell your healthcare provider if you have any side effect that bothers you or that does not go away.

These are not all the possible side effects of GaviLyte-N. For more information, ask your healthcare provider or pharmacist.

Call your doctor for medical advice about side effects. You may report side effects to FDA at 1-800-FDA-1088.

How should I store GaviLyte-N?

- Store GaviLyte-N at room temperature, between 59ºF to 86°F (15ºC to 30°C).

Keep GaviLyte-N and all medicines out of the reach of children.

General information about the safe and effective use of GaviLyte-N.

Medicines are sometimes prescribed for purposes other than those listed in a Medication Guide. Do not use GaviLyte-N for a condition for which it was not prescribed. Do not give GaviLyte-N to other people, even if they are going to have the same procedure you are. It may harm them.

This Medication Guide summarizes important information about GaviLyte-N. If you would like more information, talk with your healthcare provider. You can ask your pharmacist or healthcare provider for information that is written for healthcare professionals.

For more information, call 1-866-403-7592.

What are the ingredients in GaviLyte-N?

Active ingredients: polyethylene glycol 3350, sodium bicarbonate, sodium chloride, and potassium chloride.

Inactive ingredients: cherry flavoring, lemon flavoring, orange flavoring (flavor packs only)

LUPIN and the are registered trademarks of Lupin Pharmaceuticals, Inc.

Manufactured by:

Novel Laboratories, Inc.

Somerset, NJ 08873

Manufactured for:

Lupin Pharmaceuticals, Inc.

Naples FL, 34108

This Medication Guide has been approved by the U.S. Food and Drug Administration.

SAP Code: 276329

Rev. 11/2024

PACKAGE LABEL.PRINCIPAL DISPLAY PANEL

GaviLyte-N

Container Label

Flavor Packs (Cherry Flavor, Lemon Flavor and Orange Flavor)